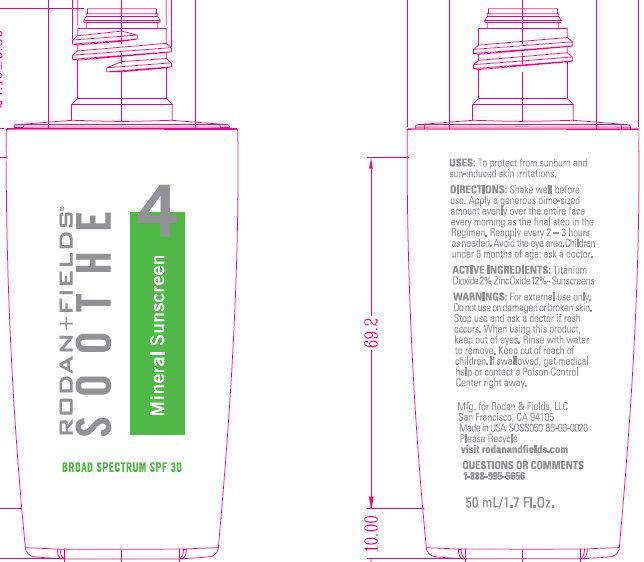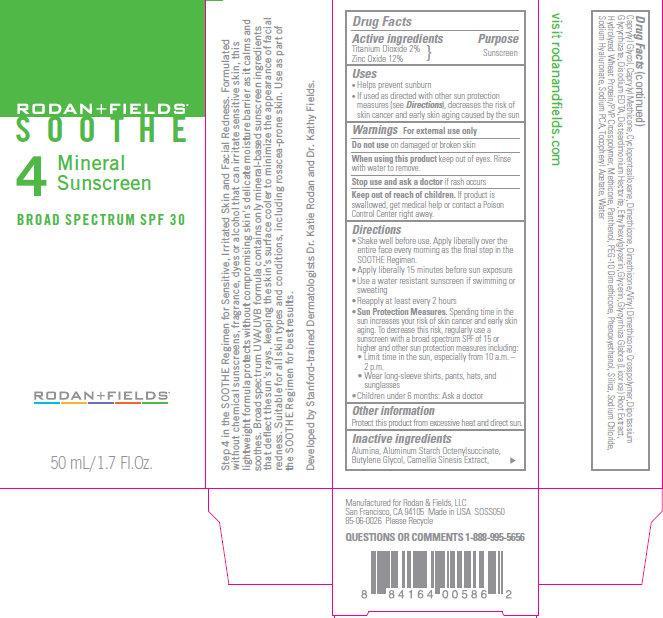 DRUG LABEL: RODAN FIELDS SOOTHE 4 Mineral Sunscreen BROAD SPECTRUM SPF 30 

NDC: 14222-0000 | Form: CREAM
Manufacturer: Rodan & Fields
Category: otc | Type: HUMAN OTC DRUG LABEL
Date: 20231212

ACTIVE INGREDIENTS: TITANIUM DIOXIDE 20 mg/1 mL; ZINC OXIDE 120 mg/1 mL
INACTIVE INGREDIENTS: ALUMINUM OXIDE; ALUMINUM STARCH OCTENYLSUCCINATE; CAMELLIA SINENSIS FLOWER; CAPRYLYL GLYCOL; CAPRYLYL TRISILOXANE; CYCLOMETHICONE 5; DIMETHICONE; DIMETHICONE/VINYL DIMETHICONE CROSSPOLYMER (SOFT PARTICLE); GLYCYRRHIZINATE DIPOTASSIUM; EDETATE DISODIUM; DISTEARDIMONIUM HECTORITE; ETHYLHEXYLGLYCERIN; GLYCERIN; LICORICE; HYDROLYZED WHEAT PROTEIN (ENZYMATIC, 3000 MW); PANTHENOL; PHENOXYETHANOL; SILICON DIOXIDE; SODIUM CHLORIDE; HYALURONATE SODIUM; SODIUM PYRROLIDONE CARBOXYLATE; .ALPHA.-TOCOPHEROL ACETATE; WATER

RODAN + FIELDS SOOTHE 4 Mineral Sunscreen BROAD SPECTRUM SPF 30

ACTIVE INGREDIENTS:

Titanium Dioxide 2% Zinc Oxide 12%

PURPOSE

Sunscreens

USES:

To protect from sunburn and sun-induced skin irritations.

WARNINGS:

For external use only.

Do not use

on damaged or broken skin.

Stop use and ask a doctor

If rash occurs.

When using this product

keep out of eyes. Rinse with water to remove.

Keep out of reach of children.

If product is swallowed, get medical help or contact a Poison Control Center right away.

DIRECTIONS:

Shake well before use. Apply a generous dime-sized amount evenly over the entire face every morning as the final step in the Regimen. Reapply every 2 - 3 hours as needed. Avoid the eye area. Children under 6 months of age: ask a doctor.

INACTIVE INGREDIENTS:

Alumina, Aluminum Starch Octenylsuccinate, Butylene Glycol, Camellia Sinesis Extract, Caprylyl Glycol, Caprylyl Methicone, Cyclopentasiloxane, Dimethicone, Dimethicone/Vinyl Dimethicone Crosspolymer, Dipotassium Glycyrrhizate, Disodium EDTA, Disteardimonium Hectorite, Ethylhexylglycerin, Glycerin, Glycyrrhiza Glabra (Licorice) Root Extract, Hydrolyzed Wheat Protein/PVP Crosspolymer, Methicone, Panthenol, PEG-10 Dimethicone, Phenoxyethanol, Silica, Sodium Chloride, Sodium Hyaluronate, Sodium PCA, Tocopheryl Acetate, Water

OTHER INFORMATION

Protect this product from excessive heat and direct sun.